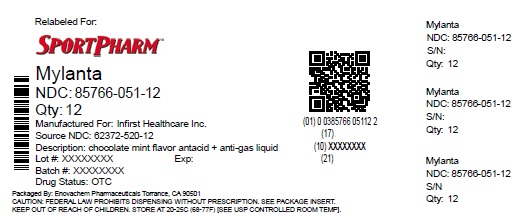 DRUG LABEL: Mylanta

NDC: 85766-051 | Form: LIQUID
Manufacturer: Sportpharm, Inc. dba Sportpharm
Category: otc | Type: HUMAN OTC DRUG LABEL
Date: 20251103

ACTIVE INGREDIENTS: CALCIUM CARBONATE 800 mg/10 mL; DIMETHICONE 80 mg/10 mL
INACTIVE INGREDIENTS: BENZYL ALCOHOL; XANTHAN GUM; SODIUM CARBONATE; CARBOXYMETHYLCELLULOSE CALCIUM; D&C RED NO. 28; MICROCRYSTALLINE CELLULOSE; WATER; SORBITOL; GLYCERIN; SUCRALOSE

All-Family Mylanta

Active ingredients

(in each 10 mL dose)

Calcium carbonate 800 mg

Simethicone Emulsion 266.6 mg/ Simethicone 80 mg

Purposes

Antacid

Anti-gas

INDICATIONS AND USAGE

Usesrelieves:

• heartburn • acid indigestion • sour stomach

• upset stomach due to thse symptoms

• pressure and bloating commonly referred to as gas

• overindulgence in food and drink

Warnings

Ask a doctor or pharmacist before useif you are presently taking a prescription drug. Antacids may interact with certain prescription drugs.

Keep out of reach of children. In case of overdose, get medical help or contact a poison control center right away at 1-800-222-1222.

Directions

• shake well before use • measure with dosing cup provided

• take as needed, between meals, at bedtime or as directed by a doctor

• do not use the maximum dosage for more than 2 weeks

• follow directions based on age below

Age | Dosage
children ages 6-11 yrs | 10 mL. Not to exceed more than 30 mL in 24 hours
adults and children 12 yrs of age and over | 10-20 mL. Not to exceed more than 60 mL in 24 hours

• mL=milliliter

Other information

• each 10 mL dose contains:

calcium 320 mg; sodium 5 mg

• store between 20-25°C (68-77°F), do not freeze

Inactive ingredients

benzyl alcohol, carboxymethylcellulose sodium, D&C red no. 28, flavor, glycerin, microcrystalline cellulose, purified water, sodium carbonate, sorbitol, sucralose, xanthan gum

Questions or comments?call 1-844-695-6624

toll free (English and Spanish)

Distributed by:

Sportpharm

2237 N Commerce Parkway,

STE 1, Weston, Florida-33326

Relabeled by:

Enovachem PHARMACEUTICALS

Torrance, CA 90501